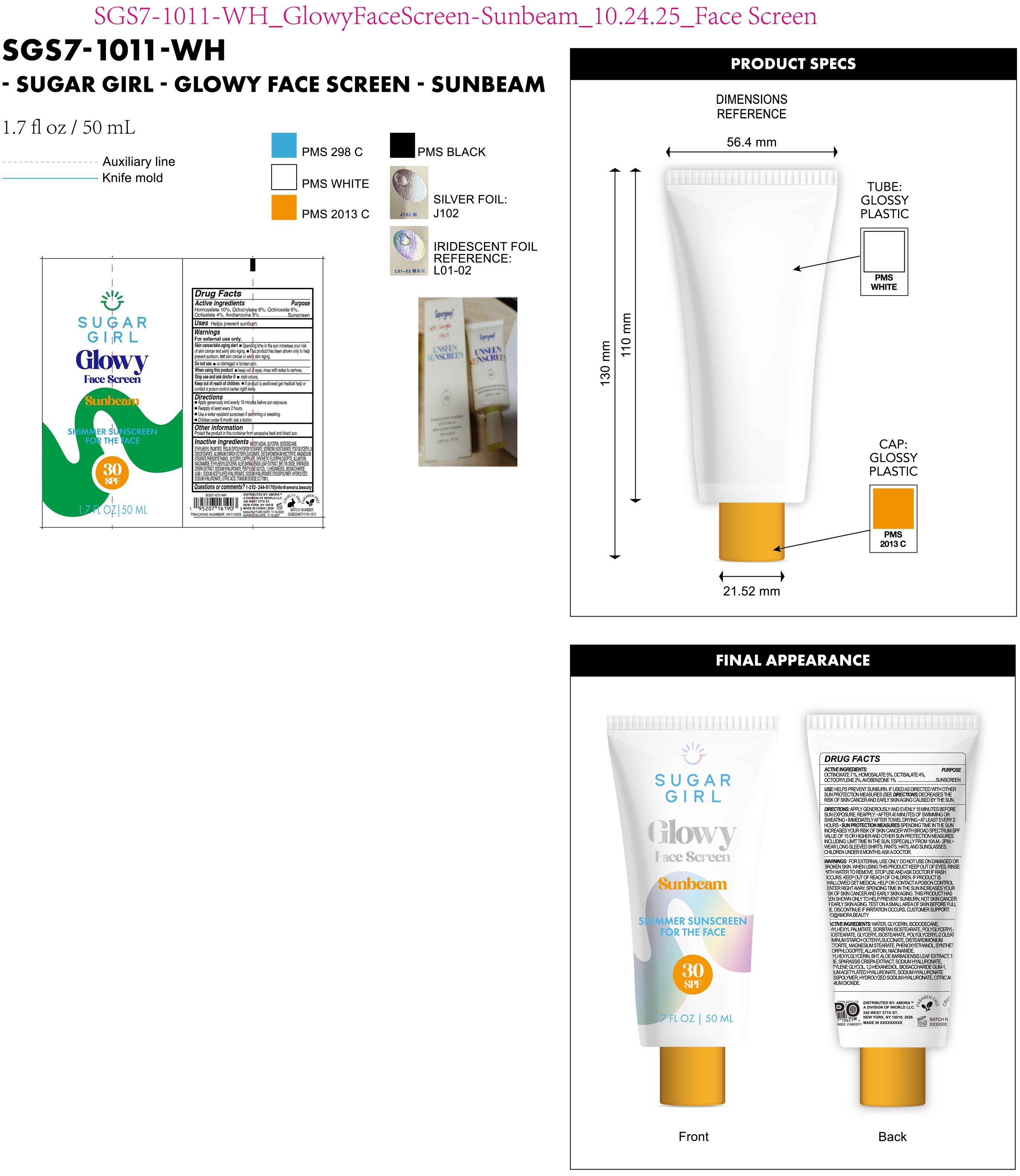 DRUG LABEL: Sugargirl Glowy Face Screen Sunbeam Shimmer Sunscreen For the Face SPF 30
NDC: 85179-036 | Form: LIQUID
Manufacturer: I World LLC
Category: otc | Type: HUMAN OTC DRUG LABEL
Date: 20260109

ACTIVE INGREDIENTS: HOMOSALATE 100 mg/1 mL; OCTOCRYLENE 80 mg/1 mL; OCTINOXATE 60 mg/1 mL; OCTISALATE 40 mg/1 mL; AVOBENZONE 30 mg/1 mL
INACTIVE INGREDIENTS: WATER; GLYCERIN; ISODODECANE; ETHYLHEXYL PALMITATE; PEG-30 DIPOLYHYDROXYSTEARATE; POLYGLYCERYL-3 DIISOSTEARATE; DISTEARDIMONIUM HECTORITE; MAGNESIUM STEARATE; PHENOXYETHANOL; GLYCERYL CAPRYLATE; ALLANTOIN; NIACINAMIDE; ETHYLHEXYLGLYCERIN; ALOE VERA LEAF; BUTYLATED HYDROXYTOLUENE; TIN OXIDE; SODIUM HYALURONATE; PENTYLENE GLYCOL; 1,2-HEXANEDIOL; BIOSACCHARIDE GUM-1; SODIUM ACETYLATED HYALURONATE; CITRIC ACID; TITANIUM DIOXIDE

Sugargirl Glowy Face Screen Sunbeam Shimmer Sunscreen For the Face SPF 30

Active Ingredients

Homosalate 10%, Octocrylene 8%, Octinoxate 6%, Octisalate 4%, Avobenzone 8%

Purpose

Sunscreen

Uses

Helps prevent sunburn.

Warnings

For external use only.

Skin cancer/skin aging alert

- Spending time in the sun increases your risk of skin cancer and early skin aging.
- This product has been shown only to help prevent sunbum, not skin cancer or early skin aging,

Do not use

- on damaged or broken skin.

When using this product

- keep out eyes. rinse with water to remove.

Stop use and ask doctor if

- rash occurs.

Keep out of reach of children.

- If product is swallowed get medical help or contact a poison control center rigiht away.

Directions

- Apply generously and evenly 15 minutes before sun exposure.
- Reapply at least every 2 hours.
- Use a water resistant sunscreen if swimming or sweating.
- Children under 6 month: ask a doctor.

Other Information

Protect the product in this container from excessive heat and direct sun.

Inactive Ingredients

WATER(AQUA), GLYCERIN, ISODODECANE, ETHYLHEXYL PALIMITATE, PEG-30 DIPOLYHYDROXYSTERATE, SORBITAN ISOSTEARATE, POLYGLYCERYL-3 DIISOSTEARATE, ALUMINIUM STARCH OCTENYLSUCOINATE, DISTEARDIMONIUM HECTORITE, MAGNESIUM STEARATE, PHENOXYETHANOL, GLYCERYL CAPRYLATE, SYNTHETIC FLUORPHLOGOPITE, ALLANTOIN, NIACINAMIDE, ETYLHEXYLGLYCERIN, ALOE BARBADENSIS LEAF EXTRACT, BHT, TIN OXIDE, SPARASSIS CRISPA EXTRACT, SODIUM HYALURONATE, PENTYLENE GLYCOL, 1,2-HEXANEDIOL, BIOSACCHARIDE GUM-1, SODIUM ACETYLATED HYALURONATE, SODIUM HYALURONATE CROSSPOLYMER, HYDROLYZED SODIUM HYALURONATE, CITRIC ACID, TITANIUM DIOXIDE (CI 77891).

Questions or comments?

1-212-244-5170 info@amora.beauty